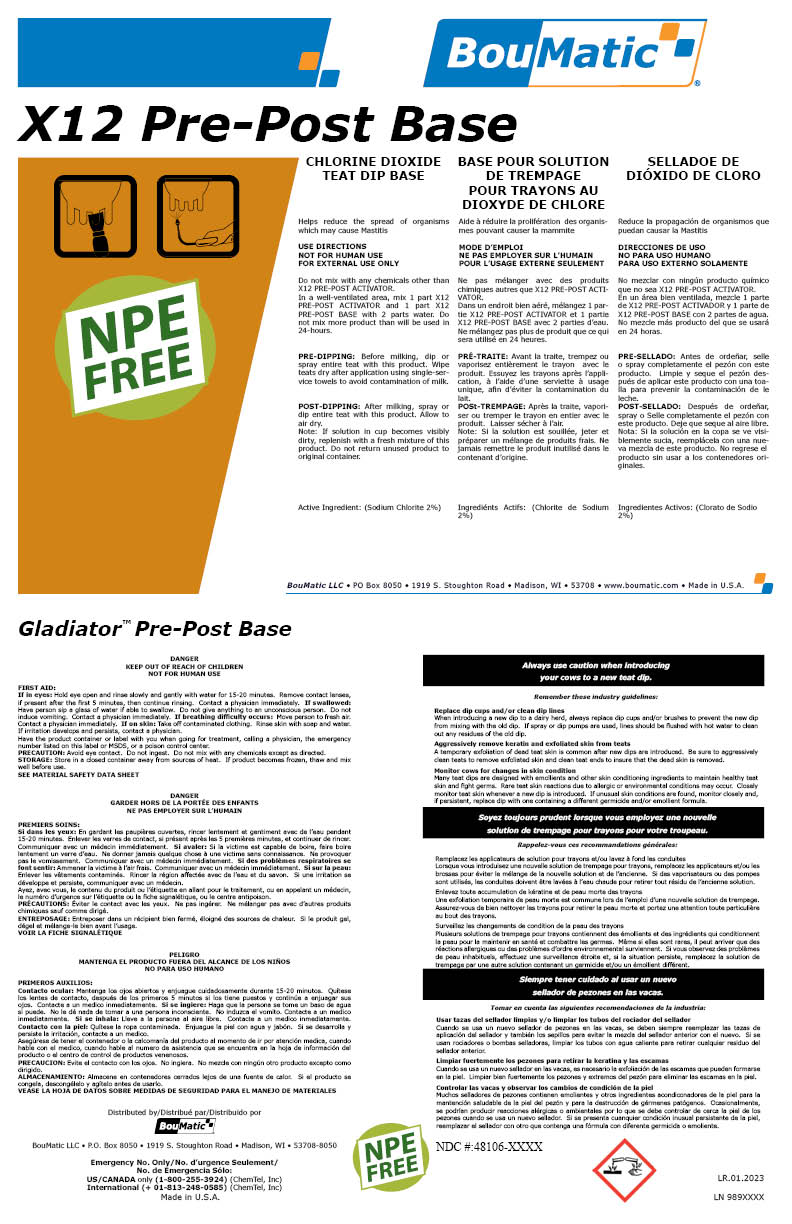 DRUG LABEL: X12 Pre-Post Base Concentrate
NDC: 48106-2049 | Form: LIQUID
Manufacturer: BOUMATIC, LLC
Category: animal | Type: OTC ANIMAL DRUG LABEL
Date: 20240812

ACTIVE INGREDIENTS: SODIUM CHLORITE 2 g/100 g

X12 Pre-Post Base

Claim of effectiveness.

Helps reduce the spread of organisms
which may cause Mastitis

Use Directions

NOT FOR HUMAN USE
FOR EXTERNAL USE ONLY
Do not mix with any chemicals other than
X12 PRE-POST ACTIVATOR.
In a well-ventilated area, mix 1 part X12
PRE-POST ACTIVATOR and 1 part X12
PRE-POST BASE with 2 parts water. Do
not mix more product than will be used
in 24-hours.

First Aid

If in eyes: Hold eye open and rinse slowly and gently with water for 15-20 minutes. Remove contact lenses,
if present after the first 5 minutes, then continue rinsing. Contact a physician immediately. If swallowed:
Have person sip a glass of water if able to swallow. Do not give anything to an unconscious person. Do not
induce vomiting. Contact a physician immediately. If breathing difficulty occurs: Move person to fresh air.
Contact a physician immediately. If on skin: Take off contaminated clothing. Rinse skin with soap and water.
If irritation develops and persists, contact a physician.
Have the product container or label with you when going for treatment, calling a physician, the emergency
number listed on this label or MSDS, or a poison control center.

Precautions & Hazards

PRECAUTION: Avoid eye contact. Do not ingest. Do not mix with any chemicals except as directed.

General Storage

STORAGE: Store in a closed container away from sources of heat. If product becomes frozen, thaw and mix
well before use.